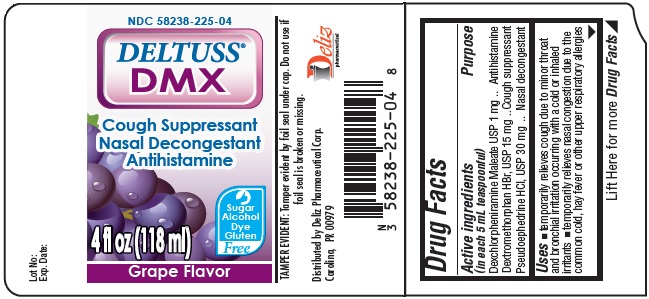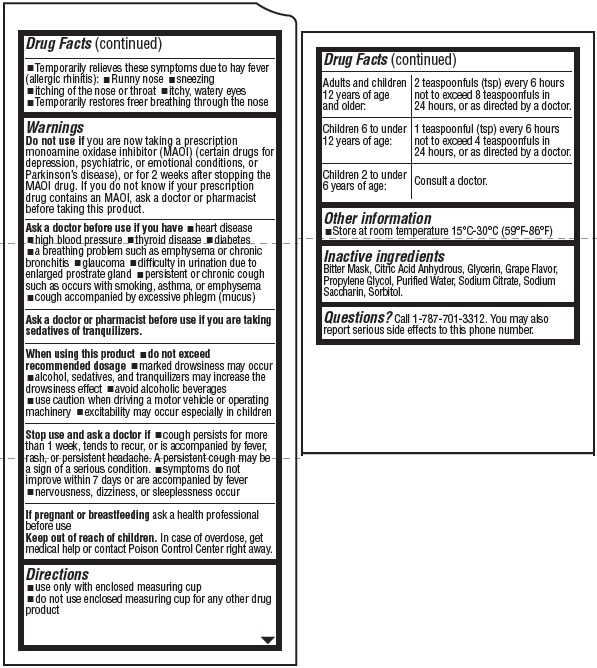 DRUG LABEL: DELTUSS DMX Cough Suppressant Nasal Decongestant Antihistamine GRAPE Flavor
NDC: 58238-225 | Form: LIQUID
Manufacturer: Deliz Pharmaceutical Corp
Category: otc | Type: HUMAN OTC DRUG LABEL
Date: 20211102

ACTIVE INGREDIENTS: DEXCHLORPHENIRAMINE MALEATE 1 mg/5 mL; DEXTROMETHORPHAN HYDROBROMIDE 15 mg/5 mL; PSEUDOEPHEDRINE HYDROCHLORIDE 30 mg/5 mL
INACTIVE INGREDIENTS: ANHYDROUS CITRIC ACID; GLYCERIN; PROPYLENE GLYCOL; WATER; SODIUM CITRATE; SACCHARIN SODIUM; SORBITOL

DELTUSS DMX Cough Suppressant Nasal Decongestant Antihistamine GRAPE Flavor

Active ingredients(in each 5 mL teaspoonful)

Dexchlorpheniramine maleate, USP 1 mg
Dextromethorphan HBr, USP 15 mg
Pseudoephedrine HCl, USP 30 mg

Purpose

Antihistamine
Cough suppressant
Nasal Decongestant

Uses

- temporarily relieves cough due to minor throat and bronchial irritation occurring with a cold or inhaled irritants
- temporarily relieves nasal congestion due to the common cold, hay fever or other upper respiratory allergies
- Temporarily relieves these symptoms due to hay fever (allergic rhinitis):
- runny nose
- sneezing
- itching of the nose or throat
- itchy, watery eyes
- Temporarily restores freer breathing through the nose

Warnings

DO NOT USE

you are now taking a prescription monoamine oxidase inhibitor (MAOI) (certain drugs for depression, psychiatric, or emotional conditions, or
Parkinson’s disease), or for 2 weeks after stopping the MAOI drug. If you do not know if your prescription drug contains an MAOI, ask a doctor or pharmacist before taking this product.

Ask a doctor before use if

you have

- heart disease
- high blood pressure
- thyroid disease
- diabetes
- a breathing problem such as emphysema or chronic bronchitis
- glaucoma
- difficulty in urination due to enlarged prostrate gland
- persistent or chronic cough such as occurs with smoking, asthma, or emphysema
- cough accompanied by excessive phlegm (mucus)

When using this product

- do not exceed recommended dosage
- marked drowsiness may occur
- alcohol, sedatives, and tranquilizers may increase the drowsiness effect
- avoid alcoholic beverages
- use caution when driving a motor vehicle or operating machinery
- excitability may occur especially in children

Stop use and ask a doctor if

- cough persists for more than 1 week, tends to recur, or is accompanied by fever, rash, or persistent headache. A persistent cough may be a sign of a serious condition.
- symptoms do not improve within 7 days or are accompanied by fever
- nervousness, dizziness, or sleeplessness occur

If pregnant or breastfeeding

ask a health professional before use.

Keep out of reach of children.

In case of overdose, get medical help or contact a Poison Control Center right away.

Directions

- use only with enclosed measuring cup
- do not use enclosed measuring cup for any other drug product

Adults and children 12 years of age and older: | 2 teaspoonfuls (tsp) every 6 hours not to exceed 8 teaspoonfuls in 24 hours, or as directed by a doctor.
Children 6 to under 12 years of age: | 1 teaspoonful (tsp) every 6 hours not to exceed 4 teaspoonfuls in 24 hours, or as directed by a doctor.
Children 2 to under 6 years of age: | Consult a doctor.

Other information

- Store at room temperature 15°C-30°C (59°F-86°F)

Inactive ingredients

Bitter Mask, Citric Acid Anhydrous, Glycerin, Grape Flavor, Propylene Glycol, Purified Water, Sodium Citrate, Sodium Saccharin, Sorbitol.

Questions?

Call 1-787-701-3312. You may also report serious side effects to this phone number.